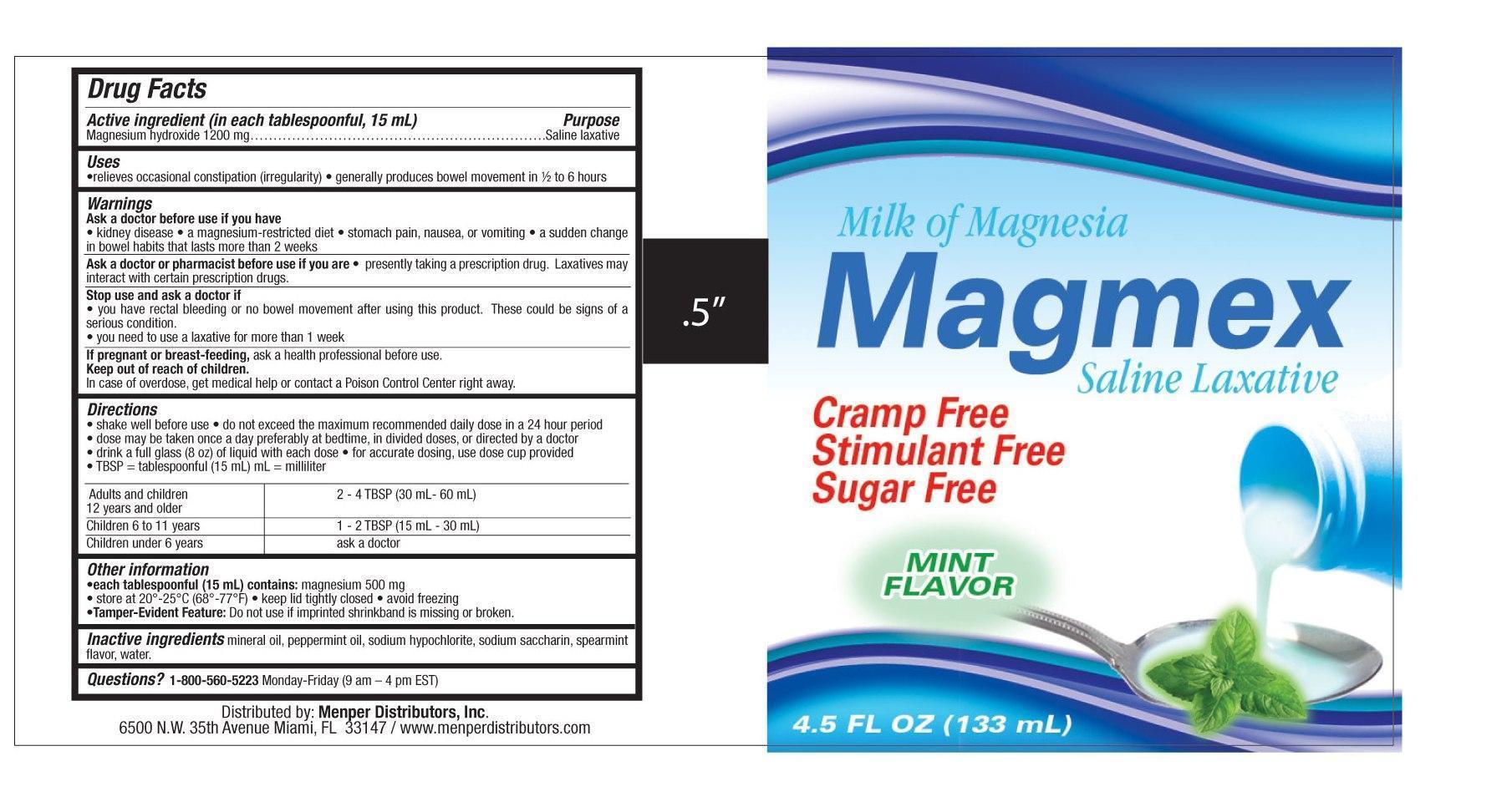 DRUG LABEL: Magmex
NDC: 53145-060 | Form: LIQUID
Manufacturer: Menper Distributors, Inc.
Category: otc | Type: HUMAN OTC DRUG LABEL
Date: 20140314

ACTIVE INGREDIENTS: MAGNESIUM HYDROXIDE 1200 mg/15 mL
INACTIVE INGREDIENTS: MINERAL OIL; PEPPERMINT OIL; SODIUM HYPOCHLORITE; SACCHARIN SODIUM; SPEARMINT; WATER

Active ingredient (in each 15 mL TBSP)

Magnesium hydroxide 1200 mg

Purpose

Saline laxative

Uses

•relieves occasional constipation (irregularity)

•generally produces bowel movement in ½ to 6 hours

Warnings

Ask a doctor before use if you have

•kidney disease

•a magnesium-restricted diet

•stomach pain, nausea, or vomiting

•a sudden change in bowel habits that lasts more than 2 weeks

Ask a doctor or pharmacist before use if you are

taking any other drug. Take this product two or more hours before or after other drugs. Laxatives may affect how other drugs work.

Stop use and ask a doctor if

•you have rectal bleeding or no bowel movement after using this product. These could be signs of a serious condition.

•you need to use a laxative for more than 1 week

If pregnant or breast-feeding,

ask a health professional before use.

Keep out of reach of children.

In case of overdose, get medical help or contact a Poison Control Center right away. (1-800-222-1222)

Directions

•shake well before use

•do not exceed the maximum recommended daily dose in a 24 hour period

•dose may be taken once a day preferably at bedtime, in divided doses, or as directed by a doctor

•drink a full glass (8 oz) of liquid with each dose•for accurate dosing, use dose cup provided

•TBSP = tablespoonful

adults and children 12 years and older

2 to 4 TBSP.

children 6 to 11 years

1 to 2 TBSP.

children under 6 years

ask a doctor

Other information

•each tablespoon (15 mL) contains: calcium 20 mg, magnesium 595 mg, and sodium 2 mg

•does not meet USP requirements for preservative effectiveness

•store at 20-25oC (68-77oF)

•keep tightly closed

•avoid freezing

Inactive ingredients

light mineral oil, peppermint oil, purified water, saccharin sodium

QUESTIONS

Questions? 1-800-560-5223 Monday-Friday 9 AM - 4 PM EST